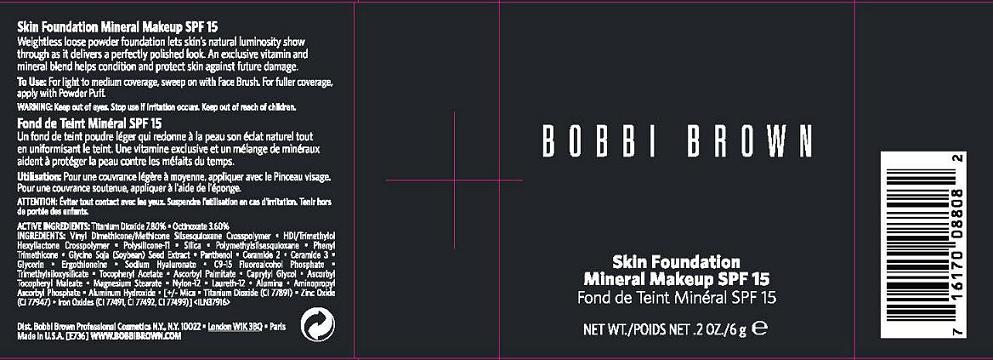 DRUG LABEL: SKIN FOUNDATION MINERAL MAKEUP
NDC: 64141-111 | Form: POWDER
Manufacturer: Bobbi Brown Professional Cosmetics Inc.
Category: otc | Type: HUMAN OTC DRUG LABEL
Date: 20110919

ACTIVE INGREDIENTS: TITANIUM DIOXIDE 7.8 g/100 g; OCTINOXATE 3.6 g/100 g
INACTIVE INGREDIENTS: POLYSILICONE-15; SILICON DIOXIDE; POLYMETHYLSILSESQUIOXANE (4.5 MICRONS); PHENYL TRIMETHICONE; SOYBEAN; PANTHENOL; CERAMIDE 2; CERAMIDE 3; GLYCERIN; ERGOTHIONEINE; HYALURONATE SODIUM; TRIMETHYLSILANE; ALPHA-TOCOPHEROL ACETATE; ASCORBYL PALMITATE; CAPRYLYL GLYCOL; MAGNESIUM STEARATE; LAURETH-12; ALUMINUM OXIDE; ALUMINUM HYDROXIDE; MICA; ZINC OXIDE; FERRIC OXIDE RED

ACTIVE INGREDIENT

ACTIVE INGREDIENTS: TITANIUM DIOXIDE 7.80% [] OCTINOXATE 3.60%

INACTIVE INGREDIENT

INACTIVE INGREDIENTS: VINYL DIMETHICONE/METHICONE SILSESQUIOXANE CROSSPOLYMER [] HDI/TRIMETHYLOL HEXYLLACTONE CROSSPOLYMER [] POLYSILICONE-11 [] SILICA [] POLYMETHYLSILSESQUIOXANE [] PHENYL TRIMETHICONE [] GLYCINE SOJA (SOYBEAN) SEED EXTRACT [] PANTHENOL [] CERAMIDE 2 [] CERAMIDE 3 [] GLYCERIN [] ERGOTHIONEINE [] SODIUM HYALURONATE [] C9-15 FLUOROALCOHOL PHOSPHATE [] TRIMETHYLSILOXYSILICATE [] TOCOPHERYL ACETATE [] ASCORBYL PALMITATE [] CAPRYLYL GLYCOL [] ASCORBYL TOCOPHERYL MALEATE [] MAGNESIUM STEARATE [] NYLON-12 [] LAURETH-12 [] ALUMINA [] AMINOPROPYL ASCORBYL PHOSPHATE [] ALUMINUM HYDROXIDE [] [+/- MICA [] TITANIUM DIOXIDE (CI 77891) [] ZINC OXIDE (CI 77947) [] IRON OXIDES (CI 77491, CI 77492, CI 77499)

WARNINGS

WARNING: KEEP OUT OF EYES. DISCONTINUE USE IF IRRITATION OCCURS. KEEP OUT OF REACH OF CHILDREN.

PACKAGE LABEL

BOBBI BROWN

SKIN FOUNDATION

MINERAL MAKEUP
SPF 15

0.2 OZ / 6 g

DISTR BOBBI BROWN PROFESSIONAL COSMETICS

NEW YORK, NY 10022